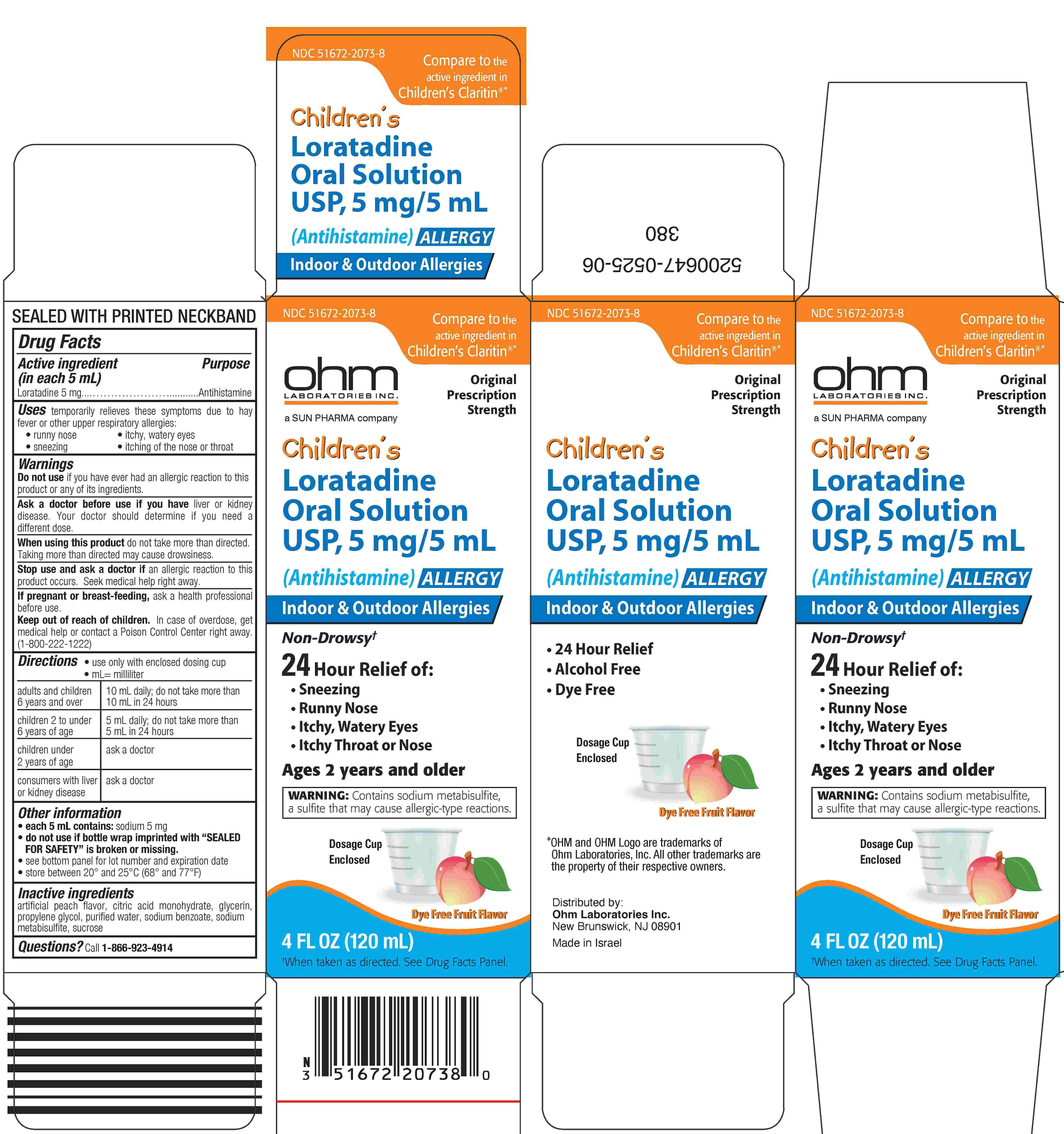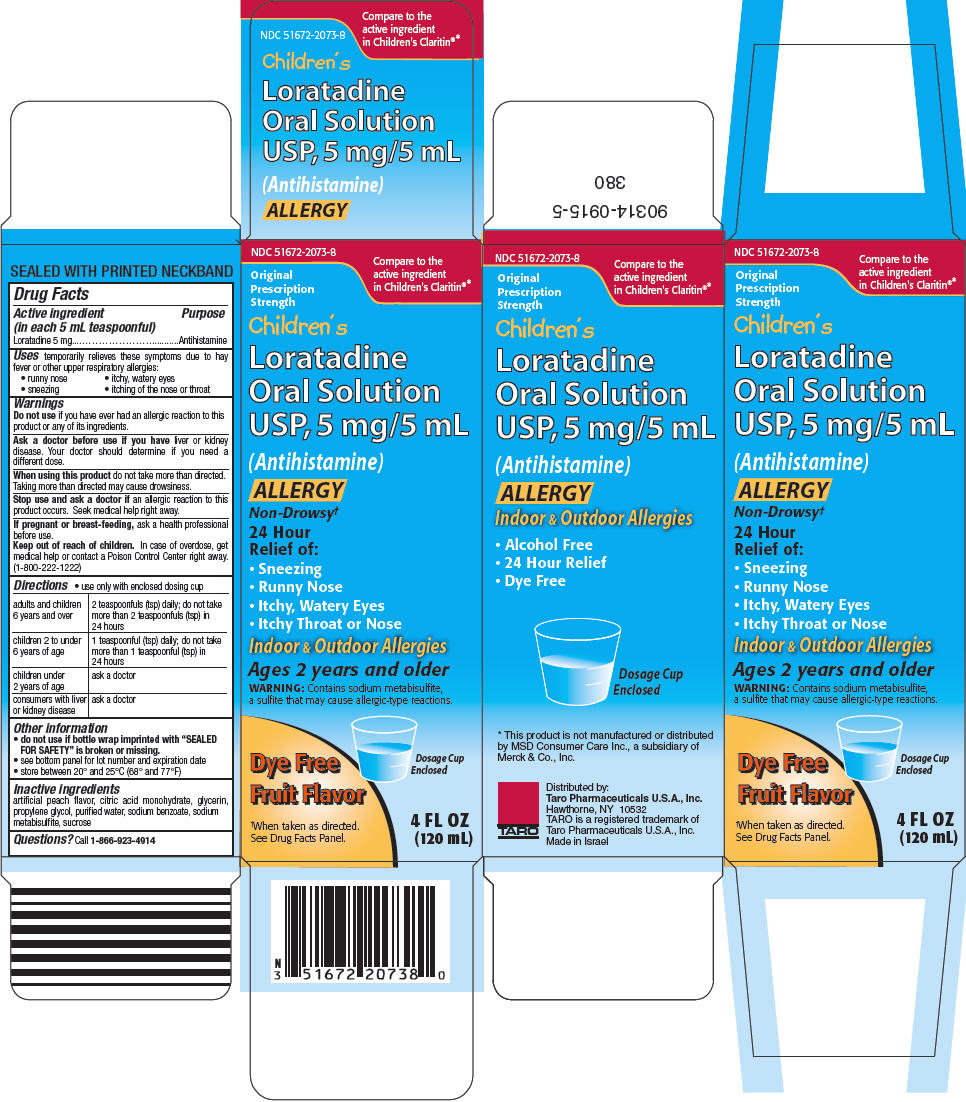 DRUG LABEL: Childrens Loratadine
NDC: 51672-2073 | Form: SOLUTION
Manufacturer: Sun Pharmaceutical Industries, Inc.
Category: otc | Type: HUMAN OTC DRUG LABEL
Date: 20250509

ACTIVE INGREDIENTS: LORATADINE 5 mg/5 mL
INACTIVE INGREDIENTS: CITRIC ACID MONOHYDRATE; GLYCERIN; PROPYLENE GLYCOL; WATER; SODIUM BENZOATE; SODIUM METABISULFITE; SUCROSE

Children's Loratadine

Drug Facts

Active ingredient (in each 5 mL)

Loratadine 5 mg

Purpose

Antihistamine

Uses

temporarily relieves these symptoms due to hay fever or other upper respiratory allergies:

- runny nose
- itchy, watery eyes
- sneezing
- itching of the nose or throat

Warnings

Do not use if you have ever had an allergic reaction to this product or any of its ingredients.

Ask a doctor before use if you have liver or kidney disease. Your doctor should determine if you need a different dose.

When using this product do not take more than directed. Taking more than directed may cause drowsiness.

Stop use and ask a doctor if an allergic reaction to this product occurs. Seek medical help right away.

PREGNANCY OR BREAST FEEDING

If pregnant or breast-feeding, ask a health professional before use.

Keep out of reach of children. In case of overdose, get medical help or contact a Poison Control Center right away. (1-800-222-1222)

Directions

- use only with enclosed dosing cup
- mL=milliliter

adults and children 6 years and over | 10 mL daily; do not take more than 10 mL in 24 hours
children 2 to under 6 years of age | 5 mL daily; do not take more than 5 mL in 24 hours
children under 2 years of age | ask a doctor
consumers with liver or kidney disease | ask a doctor

Other information

- each 5 mL contains: sodium 5 mg.
- do not use if bottle wrap imprinted with "SEALED FOR SAFETY" is broken or missing.
- see bottom panel for lot number and expiration date
- store between 20° and 25°C (68° and 77°F)

Inactive ingredients

artificial peach flavor, citric acid monohydrate, glycerin, propylene glycol, purified water, sodium benzoate, sodium metabisulfite, sucrose

Questions?

Call 1-866-923-4914

Distributed by:
Ohm Laboratories Inc.
New Brunswick, NJ 08901

Made In Israel

PRINCIPAL DISPLAY PANEL - 120 mL Bottle Carton

NDC 51672-2073-8

Children's
Loratadine
Oral Solution
USP, 5 mg/5 mL